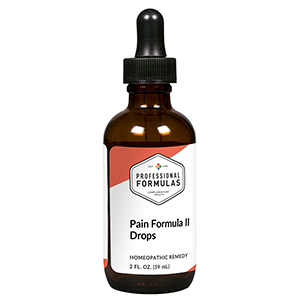 DRUG LABEL: Pain Formula II Drops
NDC: 63083-2090 | Form: LIQUID
Manufacturer: Professional Complementary Health Formulas
Category: homeopathic | Type: HUMAN OTC DRUG LABEL
Date: 20190815

ACTIVE INGREDIENTS: ZINC 3 [hp_X]/59 mL; BRYONIA ALBA ROOT 5 [hp_X]/59 mL; STRYCHNOS NUX-VOMICA SEED 6 [hp_X]/59 mL; ARSENIC TRIOXIDE 8 [hp_X]/59 mL; GELSEMIUM SEMPERVIRENS ROOT 8 [hp_X]/59 mL; LACHESIS MUTA VENOM 8 [hp_X]/59 mL; LEAD 12 [hp_X]/59 mL
INACTIVE INGREDIENTS: ALCOHOL; WATER

C90

ACTIVE INGREDIENTS

Zincum metallicum 3X
Bryonia alba 5X
Nux vomica 6X
Arsenicum album 8X
Gelsemium sempervirens 8X
Lachesis mutus 8X
Plumbum metallicum 12X

QUESTIONS

Professional Formulas

PO Box 2034 Lake Oswego, OR 97035

INDICATIONS

For the temporary relief of minor aches or pain, particularly when improved without touch, massage, or pressure.*

PURPOSE

*Claims based on traditional homeopathic practice, not accepted medical evidence. Not FDA evaluated.

WARNINGS

In case of overdose, get medical help or contact a poison control center right away.

Keep out of the reach of children.

PREGNANCY OR BREAST FEEDING

If pregnant or breastfeeding, ask a healthcare professional before use.

DIRECTIONS

Place drops under tongue 30 minutes before/after meals. Adults and children 12 years and over: Take 10 drops up to 3 times per day for up to 6 weeks. For immediate onset of symptoms, take 10 to 15 drops every 15 minutes up to 3 hours. For less severe symptoms, take 10-15 drops hourly up to 8 hours. Consult a physician for use in children under 12 years of age.

OTHER INFORMATION

Tamper resistant. If seal is broken, do not use. After opening, close container tightly and store at room temperature away from heat.

INACTIVE INGREDIENTS

20% ethanol, purified water.

LABEL

Est 1985

Professional Formulas

Complementary Health

Pain Formula II Drops

Homeopathic Remedy

2 FL. OZ. (59 mL)